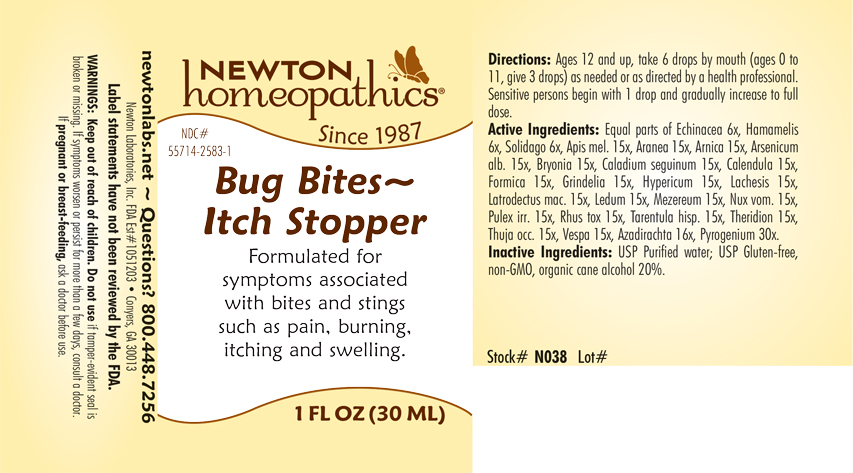 DRUG LABEL: Bug Bites - Itch Stopper
NDC: 55714-2583 | Form: LIQUID
Manufacturer: Newton Laboratories, Inc.
Category: homeopathic | Type: HUMAN OTC DRUG LABEL
Date: 20240322

ACTIVE INGREDIENTS: LYCOSA TARANTULA 15 [hp_X]/1 mL; THERIDION CURASSAVICUM 15 [hp_X]/1 mL; THUJA OCCIDENTALIS LEAFY TWIG 15 [hp_X]/1 mL; VESPA CRABRO 15 [hp_X]/1 mL; ECHINACEA, UNSPECIFIED 6 [hp_X]/1 mL; HAMAMELIS VIRGINIANA ROOT BARK/STEM BARK 6 [hp_X]/1 mL; SOLIDAGO VIRGAUREA FLOWERING TOP 6 [hp_X]/1 mL; RANCID BEEF 30 [hp_X]/1 mL; APIS MELLIFERA 15 [hp_X]/1 mL; ARANEUS DIADEMATUS 15 [hp_X]/1 mL; ARNICA MONTANA 15 [hp_X]/1 mL; ARSENIC TRIOXIDE 15 [hp_X]/1 mL; AZADIRACHTA INDICA BARK 16 [hp_X]/1 mL; BRYONIA ALBA ROOT 15 [hp_X]/1 mL; DIEFFENBACHIA SEGUINE 15 [hp_X]/1 mL; CALENDULA OFFICINALIS FLOWERING TOP 15 [hp_X]/1 mL; FORMICA RUFA 15 [hp_X]/1 mL; GRINDELIA HIRSUTULA FLOWERING TOP 15 [hp_X]/1 mL; HYPERICUM PERFORATUM 15 [hp_X]/1 mL; LACHESIS MUTA VENOM 15 [hp_X]/1 mL; LATRODECTUS MACTANS 15 [hp_X]/1 mL; LEDUM PALUSTRE TWIG 15 [hp_X]/1 mL; DAPHNE MEZEREUM BARK 15 [hp_X]/1 mL; STRYCHNOS NUX-VOMICA SEED 15 [hp_X]/1 mL; PULEX IRRITANS 15 [hp_X]/1 mL; TOXICODENDRON PUBESCENS LEAF 15 [hp_X]/1 mL
INACTIVE INGREDIENTS: WATER; ALCOHOL

Bug 2583L

OTC - KEEP OUT OF REACH OF CHILDREN SECTION

Keep out of reach of children.

OTC - PREGNANCY OR BREAST FEEDING SECTION

If pregnant or breast-feeding, ask a doctor before use.

WARNINGS SECTION

WARNINGS: Keep out of reach of children. Do not use if tamper-evident seal is broken or missing. If symptoms worsen or persist for more than a few days, consult a doctor. If pregnant or breast-feeding, ask a doctor before use.

QUESTIONS SECTION

newtonlabs.net - Questions? 800 448-7256

Newton Laboratories, Inc. FDA Est # 1051203 - Conyers, GA 30013

DOSAGE & ADMINISTRATION SECTION

Ages 12 and up take 6 drops by mouth (ages 0 to 11, give 3 drops) as needed or as directed by a health professional. Sensitive persons begin with 1 drop and gradually increast to full dose.

INACTIVE INGREDIENT SECTION

USP Purified water; USP Gluten-free non-GMO, organic cane alcohol 20%.

OTC - PURPOSE SECTION

Formulated for symptoms associated with bites and stings such as pain, burning, itching and swelling.

OTC - ACTIVE INGREDIENT SECTION

Equal parts of Echinacea 6x, Hamamelis 6x, Solidago 6x, Apis mel. 15x, Aranea 15x, Arnica 15x, Arsenicum alb. 15x, Bryonia 15x, Caladium seguinum 15x, Calendula 15, Formica 15x, Grindelia 15x, Hypericum 15x, Lachesis 15x, Latrodectus mac. 15x, Ledum 15x, Mezereum 15x, Nux vom. 15x, Pulex irr. 15x, Rhus tox. 15x, Tarentula hisp. 15x, Theridion 15x, Thuja occ. 15x, Vespa 15x, Azadirachta 16x, Pyrogenium 30x.

INDICATIONS & USAGE SECTION

Formulated for symptoms associated with bites and stings such as pain, burning, itching and swelling.